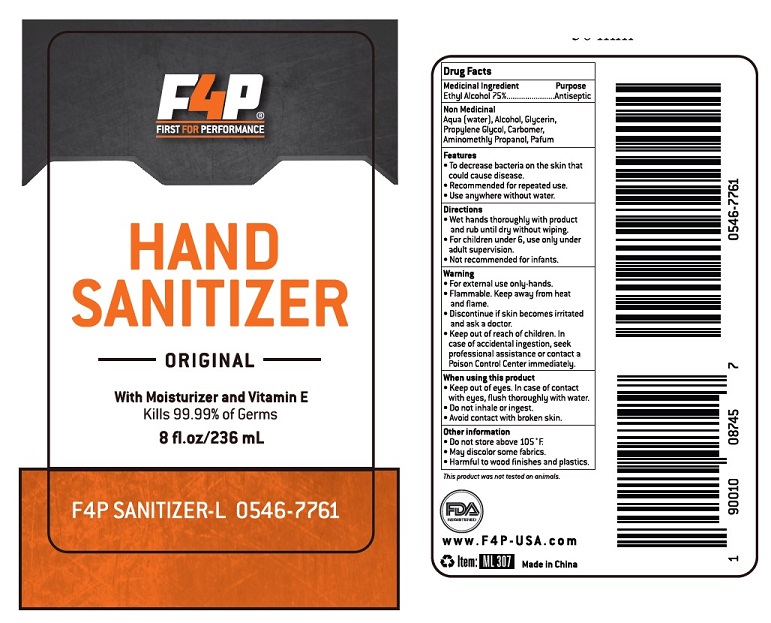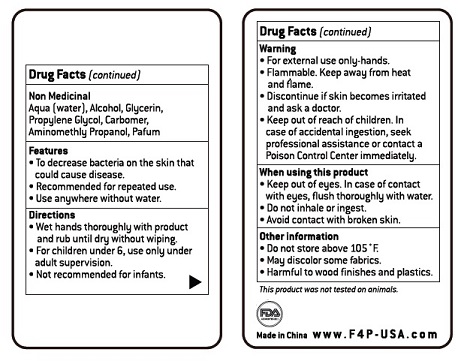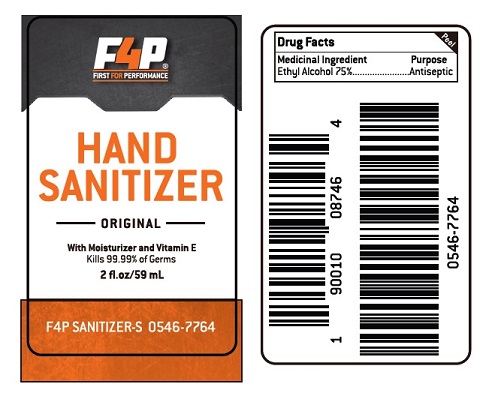 DRUG LABEL: F4P Hand Sanitizer
NDC: 74970-001 | Form: LIQUID
Manufacturer: CITY ELECTRIC SUPPLY COMPANY DBA F4P
Category: otc | Type: HUMAN OTC DRUG LABEL
Date: 20221014

ACTIVE INGREDIENTS: ALCOHOL 75 mL/100 mL
INACTIVE INGREDIENTS: GLYCERIN; PROPYLENE GLYCOL; WATER; AMINOMETHYLPROPANOL; CARBOMER HOMOPOLYMER TYPE C

Active Ingredient

Alcohol 75% v/v.

Purpose

Antiseptic

Usage

To decrease bacteria on skin that could cause disease Recommended for repeated use

Use anywhere without water

Warnings

For external use only-hands

- Flammable. Keep away from heat and flame.
- Discontinue if skin becomes irritated and ask a doctor.

- Keep out of reach of children. In case of accidental ingestion, seek professional assistance or contact a Poison Control Center immediately.

Directions

Wet hands thoroughly with product and rub until dry without wiping.
For children under 6, use only with adult supervision.
Not recommended for infants.

Inactive ingredients

Aqua (water), Glycerin, Propylene glycol, Alcohol, Carbomer, Aminomethly Propanol, Parfume

Package Label - 59 mL & 236 mL

59 mL label front

59 mL labe back

Label 236 mL